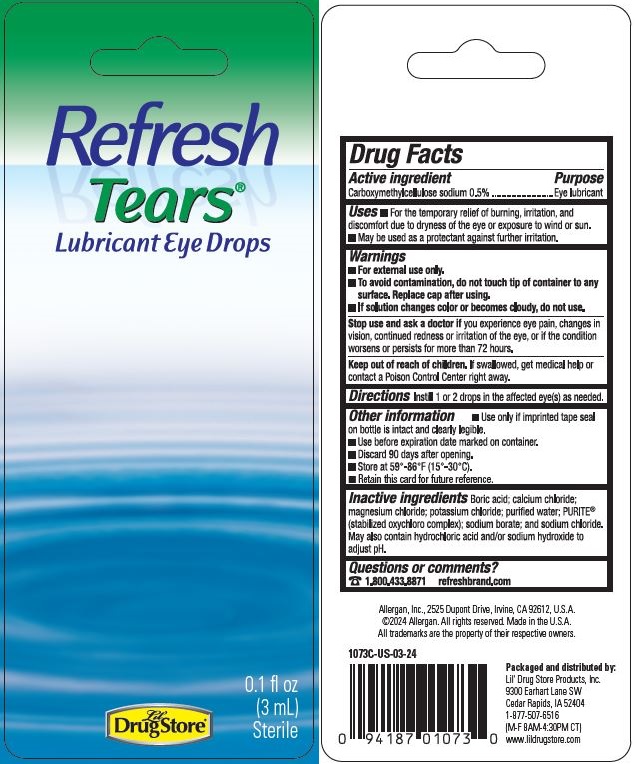 DRUG LABEL: Refresh Tears
NDC: 66715-1073 | Form: LIQUID
Manufacturer: Lil' Drug Store Products, Inc.
Category: otc | Type: HUMAN OTC DRUG LABEL
Date: 20251125

ACTIVE INGREDIENTS: CARBOXYMETHYLCELLULOSE SODIUM 5 mg/1 mL
INACTIVE INGREDIENTS: WATER; SODIUM CHLORIDE; BORIC ACID; SODIUM CHLORITE; MAGNESIUM CHLORIDE; POTASSIUM CHLORIDE; CHLORINE DIOXIDE; SODIUM BORATE; SODIUM CHLORATE; HYDROCHLORIC ACID; SODIUM HYDROXIDE; CALCIUM CHLORIDE

Refresh Tears

Drug Facts

Active ingredient

Carboxymethylcellulose sodium 0.5%

Purpose

Eye lubricant

Uses

- For the temporary relief of burning, irritation, and discomfort due to dryness of the eye or exposure to wind or sun.
- May be used as a protectant against further irritation.

Warnings

- For external use only.
- To avoid contamination, do not touch tip of container to anysurface. Replace cap after using.
- If solution changes color or becomes cloudy, do not use.

Stop use and ask a doctor if you experience eye pain, changes in vision, continued redness or irritation of the eye, or ff the condition
worsens or persists for more than 72 hours.

Keep out of reach of children. H swailowed, get medical help or contact a Poison Control Center right away.

Directions

Instill 1 or 2 droos in the affected evelsl as needed.

Other information

- Use only if imprinted tape seal on bottle is intact and clearly legible.
- Use before expiration date marked on container.
- Discard 90 days after opening.
- Store at 59°-86°F (15°-30°C).
- Retain this card for future reference.

Inactive ingredients

Boric acid; calcium chloride; magne~um chloride; pctassium chloride; purified water; PURITE® (stabilized oxychloro complex); sodium borate; and sodium chloride.May also contain hydrochloric acid and/or sodium hydroxide to adjust pH.

Questions or comments

1.800.433.8871 relrashbrand.com

Allergan, Inc., 2525 Dupont Drive, Irvine, CA 92612, U.S.A.
©2024 Allergan. All rights reserved. Made in the U.S.A.
All trademarks are the property of their respective owners.

Packaged and distributed by:
Lil' Drug Store Products, Inc.
9300 Earhart Lane SW
Cedar Rapids, IA 52404
1-877-507-6516
(M-F 8AM-4:30PM CT)
www.lildrugstore.com

Refresh Tears® Backing Card

Refresh

Tears®

Lubricant Eye Drops

[Lil' Drug Store logo]

0.1 fl oz

(3 mL)

Sterile